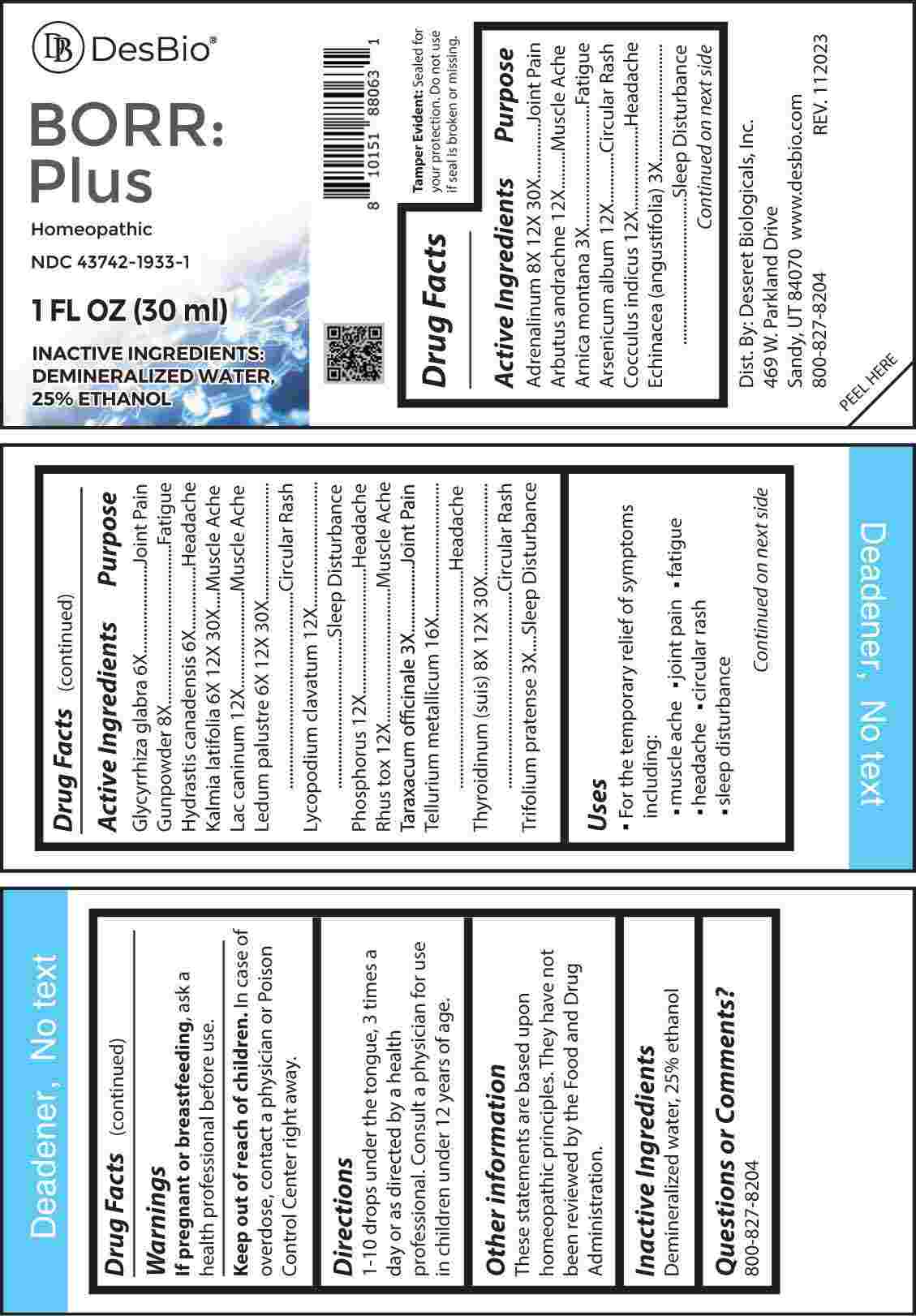 DRUG LABEL: BORR PLUS
NDC: 43742-1933 | Form: LIQUID
Manufacturer: Deseret Biologicals, Inc.
Category: homeopathic | Type: HUMAN OTC DRUG LABEL
Date: 20240227

ACTIVE INGREDIENTS: ARNICA MONTANA WHOLE 3 [hp_X]/1 mL; ECHINACEA ANGUSTIFOLIA WHOLE 3 [hp_X]/1 mL; TARAXACUM OFFICINALE 3 [hp_X]/1 mL; TRIFOLIUM PRATENSE FLOWER 3 [hp_X]/1 mL; GLYCYRRHIZA GLABRA 6 [hp_X]/1 mL; GOLDENSEAL 6 [hp_X]/1 mL; KALMIA LATIFOLIA LEAF 6 [hp_X]/1 mL; RHODODENDRON TOMENTOSUM LEAFY TWIG 6 [hp_X]/1 mL; ACTIVATED CHARCOAL 8 [hp_X]/1 mL; EPINEPHRINE 8 [hp_X]/1 mL; SUS SCROFA THYROID 8 [hp_X]/1 mL; ARBUTUS ANDRACHNE LEAFY SHOOT 12 [hp_X]/1 mL; ARSENIC TRIOXIDE 12 [hp_X]/1 mL; ANAMIRTA COCCULUS SEED 12 [hp_X]/1 mL; CANIS LUPUS FAMILIARIS MILK 12 [hp_X]/1 mL; LYCOPODIUM CLAVATUM SPORE 12 [hp_X]/1 mL; PHOSPHORUS 12 [hp_X]/1 mL; TOXICODENDRON PUBESCENS LEAF 12 [hp_X]/1 mL; TELLURIUM 16 [hp_X]/1 mL
INACTIVE INGREDIENTS: WATER; ALCOHOL

DRUG FACTS:

ACTIVE INGREDIENTS:

Adrenalinum 8X, 12X, 30X, Arbutus Andrachne 12X, Arnica Montana 3X, Arsenicum Album 12X, Cocculus Indicus 12X, Echinacea (Angustifolia) 3X, Glycyrrhiza Glabra 6X, Gunpowder 8X, Hydrastis Canadensis 6X, Kalmia Latifolia 6X, 12X 30X, Lac Caninum 12X, Ledum Palustre 6X, 12X, 30X, Lycopodium Clavatum 12X, Phosphorus 12X, Rhus Tox 12X, Taraxacum Officinale 3X, Tellurium Metallicum 16X, Thyroidinum (Suis) 8X, 12X, 30X, Trifolium Pratense 3X.

PURPOSE:

Adrenalinum – Joint Pain, Arbutus Andrachne – Muscle Ache, Arnica Montana - Fatigue, Arsenicum Album – Circular Rash, Cocculus Indicus - Headache, Echinacea (Angustifolia) – Sleep Disturbance, Glycyrrhiza Glabra – Joint Pain, Gunpowder - Fatigue, Hydrastis Canadensis - Headache, Kalmia Latifolia – Muscle Ache, Lac Caninum – Muscle Ache, Ledum Palustre – Circular Rash, Lycopodium Clavatum – Sleep Disturbance, Phosphorus - Headache, Rhus Tox – Muscle Ache, Taraxacum Officinale – Joint Pain, Tellurium Metallicum - Headache, Thyroidinum (Suis) – Circular Rash, Trifolium Pratense – Sleep Disturbance

USES:

• For the temporary relief of symptoms including:

• muscle aches • joint pain • fatigue

• headache • circular rash

• sleep disturbance

These statements are based upon homeopathic principles. They have not been reviewed by the Food and Drug Administration.

WARNINGS:

If pregnant or breast-feeding, ask a health professional before use.

Keep out of reach of children. In case of overdose, contact a physician or Poison Control Center right away.

Tamper Evident: Sealed for your protection. Do not use if seal is broken or missing.

KEEP OUT OF REACH OF CHILDREN:

In case of overdose, contact a physician or Poison Control Center right away.

DIRECTIONS:

1-10 drops under the tongue, 3 times a day or as directed by a health professional. Consult a physician for use in children under 12 years of age.

INACTIVE INGREDIENTS:

Demineralized water, 25% ethanol

QUESTIONS:

Dist. By: Deseret Biologicals, Inc.
469 W. Parkland Drive
Sandy, UT 84070

www.desbio.com

800-827-8204

PACKAGE LABEL DISPLAY:

Des Bio

BORR:Plus

Homeopathic

NDC 43742-1933-1

1 FL OZ (30 ml)